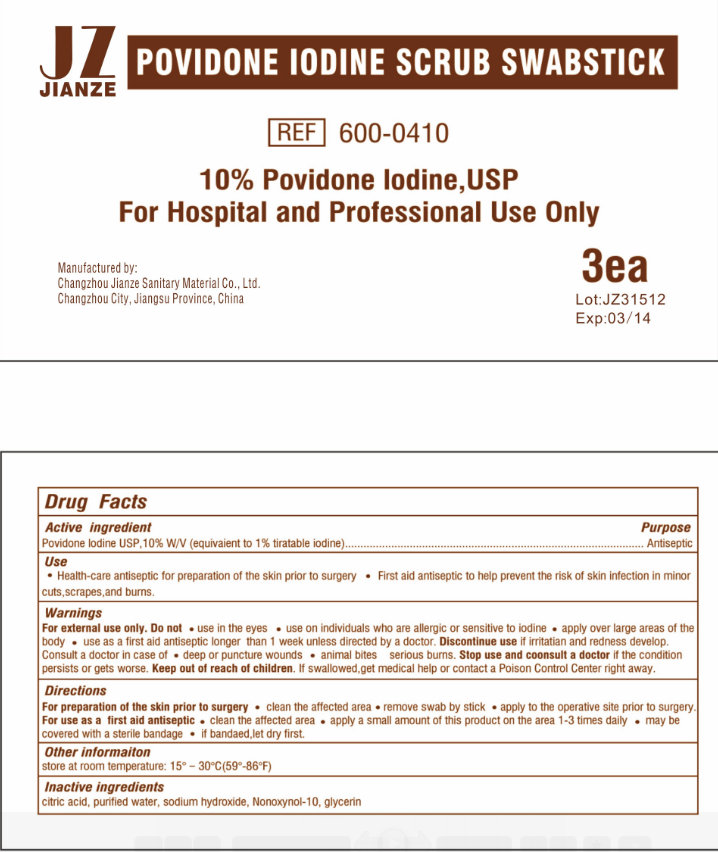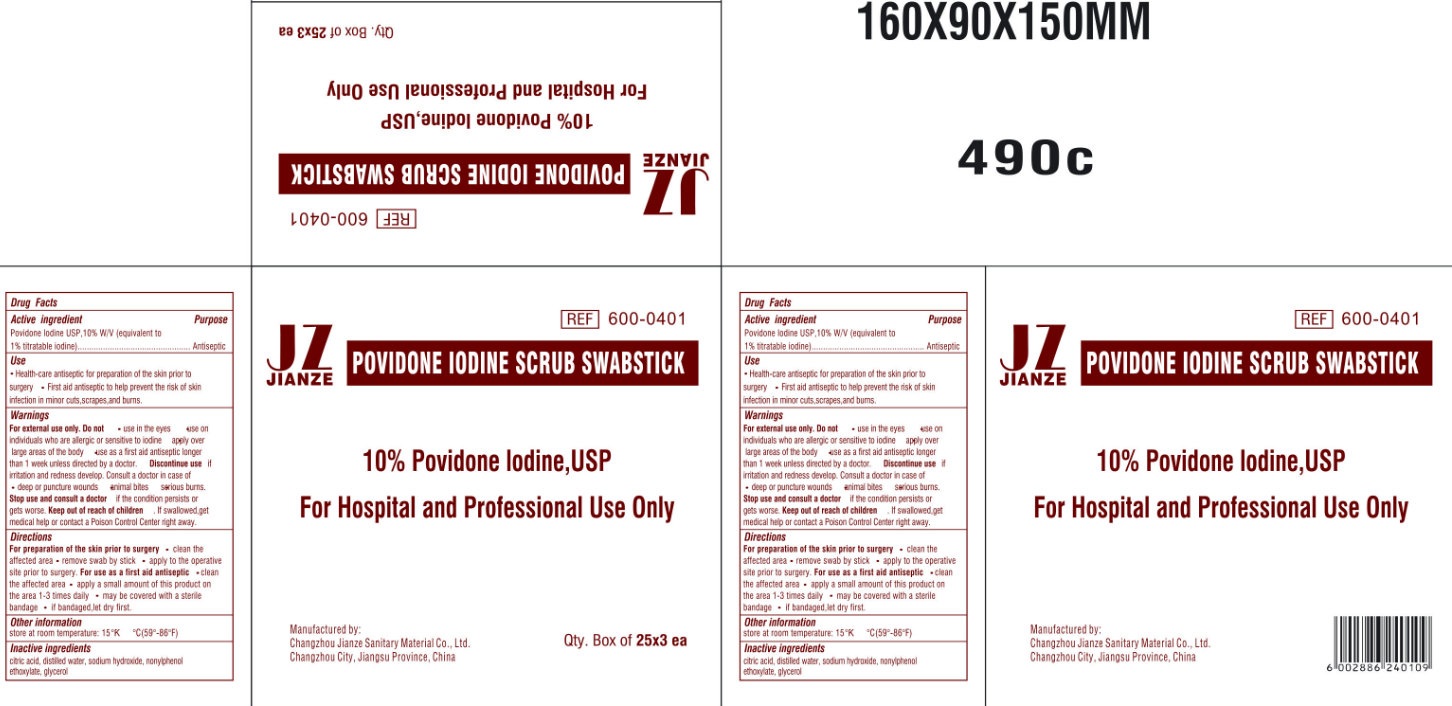 DRUG LABEL: JIANZE POVIDONE IODINE SCRUB
NDC: 50666-006 | Form: LIQUID
Manufacturer: Changzhou Jianze Sanitary Material Co., Ltd.
Category: otc | Type: HUMAN OTC DRUG LABEL
Date: 20120620

ACTIVE INGREDIENTS: POVIDONE-IODINE 10 g/100 g
INACTIVE INGREDIENTS: CITRIC ACID MONOHYDRATE; WATER; SODIUM HYDROXIDE; NONOXYNOL-10; GLYCERIN

JIANZE POVIDONE IODINE SCRUB SWABSTICK

ACTIVE INGREDIENT

Povidone Iodine USP, 10% W/V (equivalent to 1% tiratable iodine)

PURPOSE

Antiseptic

USE:

- Health-care antiseptic for preparation of the skin prior to surgery
- First aid antiseptic to help prevent the risk of skin infection in minor cuts, scrapes, and burns.

WARNINGS:

For External Use Only
Do not

- use on the eyes
- use on individuals who are allergic or sensitive to iodine
- apply over large area of the body
- use as a first aid antiseptic longer than 1 week unless directed by a doctor.

Discontinue use if irritation and redness develop
Consult a doctor in case of

- deep or puncture wounds
- animal bites
- serious burns

STOP USE AND CONSULT A DOCTOR

it the condition persists or gets worse.

KEEP OUT OF REACH OF CHILDREN.

In swallowed get medical help or contact a Poison Control Center right away.

DIRECTIONS

For preparation of the skin prior to surgery

- Clean the affected area
- Remove swab by stick
- Apply to the operative site prior to surgery.

For use as a first aid antiseptic

- Clean the affected area
- Apply a small amount of this product on the area 1-3 times daily
- May be covered with a sterile bandage
- If bandaged, let dry first.

OTHER INFORMATION

Store at room temperature 15 degrees - 30 degrees C (59 degrees - 86 degrees F)

INACTIVE INGREDIENTS:

Citric Acid, Purified Water, Sodium Hydroxide, Nonoxynol-10, Glycerin